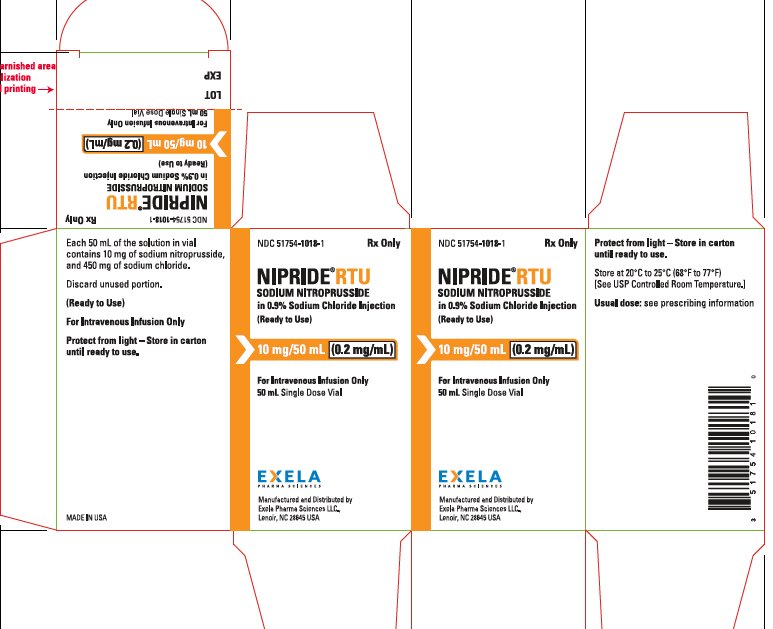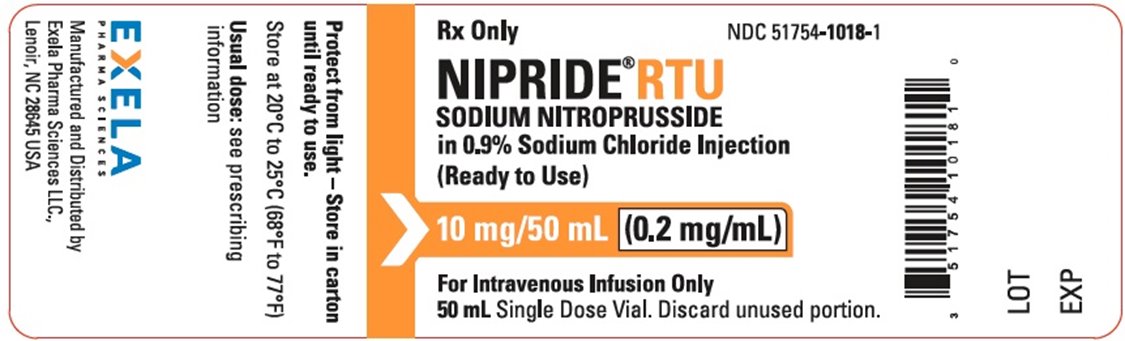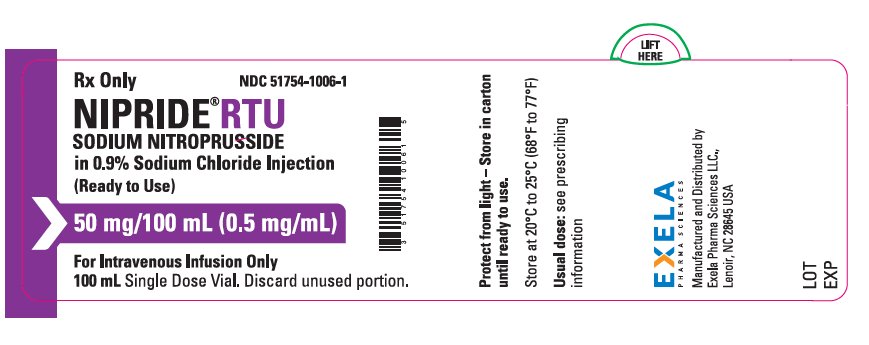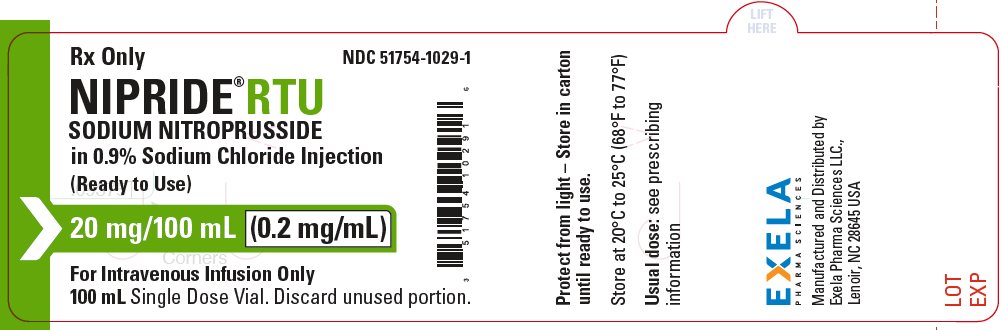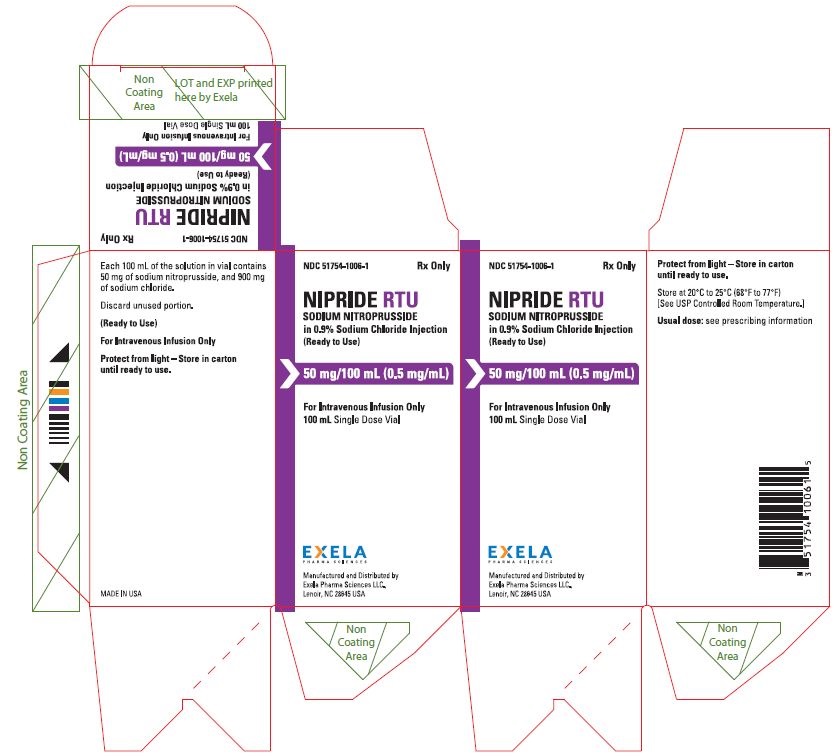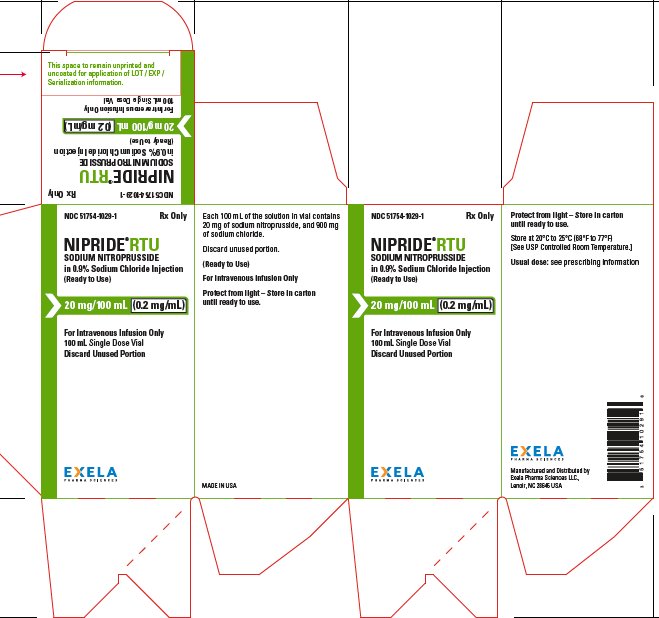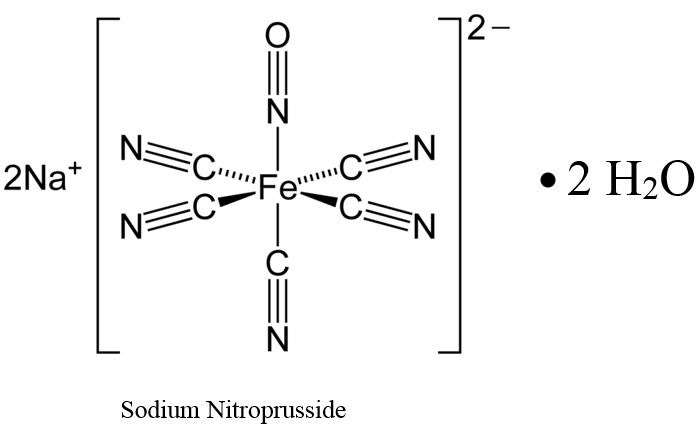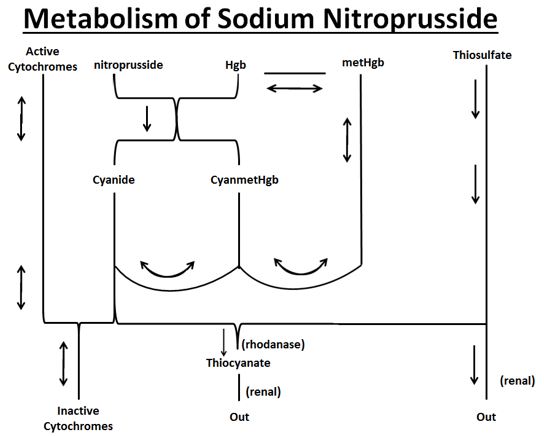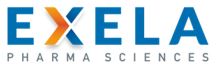 DRUG LABEL: NIPRIDE RTU
NDC: 51754-1006 | Form: INJECTION, SOLUTION
Manufacturer: EXELA PHARMA SCIENCES, LLC
Category: prescription | Type: HUMAN PRESCRIPTION DRUG LABEL
Date: 20180720

ACTIVE INGREDIENTS: SODIUM NITROPRUSSIDE 0.5 mg/1 mL
INACTIVE INGREDIENTS: SODIUM CHLORIDE 900 mg/1 mL; WATER

HIGHLIGHTS OF PRESCRIBING INFORMATION

These highlights do not include all the information needed to use NIPRIDE® RTU safely and effectively. See full prescribing information for NIPRIDE® RTU.
NIPRIDE® RTU, for intravenous use
Initial U.S. Approval: 1988

WARNING: (A) EXCESSIVE HYPOTENSION; (B) CYANIDE TOXICITY

(A) Sodium Nitroprusside can cause precipitous decreases in blood pressure which can lead to irreversible ischemic injuries or death. Use only with continuous blood pressure monitoring. (2.2, 5.1)

(B) Sodium nitroprusside metabolism produces dose-related cyanide, which can be lethal. A patient’s ability to buffer cyanide will be exceeded in less than one hour at the maximum dose rate (10 mcg/kg/min); limit infusion at the maximum rate to as short a duration as possible (5.2).

1 INDICATIONS AND USAGE

Sodium nitroprusside is a direct acting vasodilator indicated for:

- Immediate reduction of blood pressure (1.1)
- Producing controlled hypotension to reduce bleeding during surgery. (1.2)
- Treatment of acute heart failure to reduce left ventricular end-diastolic pressure, pulmonary capillary wedge pressure, peripheral vascular resistance and mean arterial blood pressure. (1.3)

2 DOSAGE AND ADMINISTRATION

Initiate infusion of sodium nitroprusside at a rate of 0.3 mcg/kg/min, and titrate every few minutes until the desired effect is achieved OR the maximum recommended infusion rate of 10 mcg/kg/min has been reached (2.2).

3 DOSAGE FORMS AND STRENGTHS

Injection: 50 mg of sodium nitroprusside in 100 mL of 0.9% sodium chloride (0.5 mg/mL) in 100 mL single-use vials, 20 mg of sodium nitroprusside in 100 mL of 0.9% sodium chloride (0.2 mg/mL) in 100 mL single-use vials and 10 mg of sodium nitroprusside in 50 mL of 0.9% sodium chloride (0.2 mg/mL) in 50 mL single-use vials (3).

4 CONTRAINDICATIONS

- Diseases with compensatory hypertension (e.g. coarctation of the aorta, arteriovenous shunting) (4).
- Inadequate cerebral circulation or moribund patients (A.S.A. Class 5E) coming to emergency surgery (4).
- Congenital (Leber’s) optic atrophy or tobacco amblyopia (4).
- Acute heart failure with reduced peripheral vascular resistance (4).
- Concomitant use with sildenafil, tadalafil, vardenifil, or riociguat (4)

5 WARNINGS AND PRECAUTIONS

- Thiocynate toxicity (5.3)
- Methemoglobinemia (5.4)
- Increases in intracranial pressure (5.5)
- Diminished capacity to compensate for anemia and hypovolemia with anesthesia during surgery (5.6)

6 ADVERSE REACTIONS

Most common adverse reactions are hypotension and cyanide toxicity (6).

To report SUSPECTED ADVERSE REACTIONS, Contact Exela Pharma Sciences, LLC at 1-888-451-4321 or FDA at 1-800-FDA-1088 or www.fda.gov/medwatch.

FULL PRESCRIBING INFORMATION

WARNING: (A) EXCESSIVE HYPOTENSION; (B) CYANIDE TOXICITY

(A) EXCESSIVE HYPOTENSION:

Sodium Nitroprusside can cause precipitous decreases in blood pressure which can lead to irreversible ischemic injuries or death. Use only with continuous blood pressure monitoring [see Dosage and Administration (2.2) and Warnings and Precautions (5.1).

(B) CYANIDE TOXICITY:

Sodium nitroprusside metabolism produces dose-related cyanide, which can be lethal. A patient’s ability to buffer cyanide will be exceeded in less than one hour at the maximum dose rate (10 mcg/kg/min); limit infusions at the maximum rate to as short a duration as possible [see Warnings and Precautions (5.2)].

1 INDICATIONS AND USAGE

1.1 Immediate Reduction of Blood Pressure

Sodium nitroprusside is indicated for the immediate reduction of blood pressure of adult and pediatric patients in hypertensive crises.

1.2 Induction and Maintenance of Controlled Hypotension

Sodium nitroprusside indicated for induction and maintenance of controlled hypotension in adults and children during surgery, to reduce bleeding.

1.3 Treatment of Acute Heart Failure

Sodium nitroprusside is indicated for the treatment of acute heart failure to reduce, left ventricular end-diastolic pressure, pulmonary capillary wedge pressure, peripheral vascular resistance and mean arterial blood pressure.

2 DOSAGE AND ADMINISTRATION

2.1 Inspection

Inspect parenteral drug products for particulate matter and discoloration prior to administration, whenever solution and container permit. Sodium nitroprusside should be a clear colorless to red/brown color; do not use if solution is blue, green, or bright red.

2.2 Dosing

Continuously monitor blood pressure in patients receiving sodium nitroprusside. Start infusion of sodium nitroprusside at a rate of 0.3 mcg/kg/min. Evaluate blood pressure for at least 5 minutes before titrating to a higher or lower dose to achieve the desired blood pressure. The dose may be titrated upward until:

- the desired effect is achieved,
- systemic blood pressure cannot be further reduced without compromising the perfusion of vital organs, or
- the maximum recommended infusion rate of 10 mcg/kg/min has been reached, whichever occurs first.

In patients with eGFR <30 mL/min/1.73 m^2, limit the mean infusion rate to less than 3 mcg/kg/min. In anuric patients, limit the mean infusion rate to 1 mcg/kg/min.

2.3 Administration

Do not administer other drugs in the same solution with sodium nitroprusside.

Sodium nitroprusside must be delivered by a volumetric infusion pump because small variations in infusion rate can lead to wide, undesirable variations in blood pressure [see Clinical Pharmacology (12.2)].

3 DOSAGE FORMS AND STRENGTHS

Injection: 50 mg/100 mL of 0.9% sodium chloride (0.5 mg/mL), 20 mg/100 mL of 0.9% sodium chloride (0.2 mg/mL), and 10 mg/50 mL of 0.9% sodium chloride (0.2 mg/mL). NIPRIDE® RTU is supplied as a sterile, unpreserved, colorless to red-brown solution available in a single-use vial.

4 CONTRAINDICATIONS

- Diseases with compensatory hypertension (e.g., coarctation of the aorta, arteriovenous shunting).
- Inadequate cerebral circulation or in moribund patients (A.S.A. Class 5E) coming to emergency surgery.
- Patients with congenital (Leber’s) optic atrophy or with tobacco amblyopia.
- Acute heart failure associated with reduced peripheral vascular resistance.
- Concomitant use with sildenafil, tadalafil, vardenifil, or riociguat.

5 WARNINGS AND PRECAUTIONS

5.1 Excessive Hypotension

Sodium nitroprusside, can cause excessive hypotension leading to hypoperfusion of vital organs. Hypotension should resolve within 1-10 minutes after discontinuation of the nitroprusside infusion; during these few minutes, it may be helpful to put the patient into a head-down (Trendelenburg) position to maximize venous return. If hypotension persists more than a few minutes after discontinuation, consider other causes. Elderly patients may be more sensitive to the hypotensive effects of the drug.

5.2 Cyanide Toxicity

Sodium nitroprusside infusions above 2 mcg/kg/min generate cyanide ion (CN¯) faster than the body can normally dispose of it. At the maximum recommended infusion rate of 10 mcg/kg/min, the patient’s ability to buffer CN¯ will be exceeded in less than one hour [see Overdose (10)].

Patients with hepatic dysfunction are more susceptible to cyanide toxicity.

An early manifestation of cyanide toxicity is increasing dosage requirements to maintain blood pressure control. Metabolic acidosis may not be evident for more than an hour after toxic cyanide levels accumulate.

If cyanide toxicity develops, discontinue sodium nitroprusside, and consider specific treatment of cyanide toxicity [see Overdosage (10)].

5.3 Thiocyanate Toxicity

Most of the cyanide produced during metabolism of sodium nitroprusside is eliminated in the form of thiocyanate. Thiocyanate is mildly neurotoxic (tinnitus, miosis, hyperreflexia) at serum levels of 1 mmol/L (60 mg/L). Thiocyanate is life-threatening when levels reach ~200 mg/L. Therefore, routine monitoring of plasma thiocyanate levels is recommended in patients with normal renal function when cumulative sodium nitroprusside doses exceed 7 mg/kg/day. In patients with eGFR <30 mL/min/1.73 m2, limit the mean infusion rate to less than 3 mcg/kg/min. In anuric patients, limit the mean infusion rate to 1 mcg/kg/min.

Renal hemodialysis may be used to eliminate thiocyanate in cases of severe toxicity.

5.4 Methemoglobinemia

Sodium nitroprusside infusions cause conversion of hemoglobin to methemoglobin in a dose-dependent manner. Methemoglobin binds oxygen more strongly than does hemoglobin, and when methemoglobin levels are elevated, oxygen release from red blood cells in tissue capillaries may be impaired. However, conversion of methemoglobin back to hemoglobin is normally rapid, and clinically significant methemoglobinemia is infrequent.

Suspect methemoglobinemia in patients who have received >10 mg/kg of sodium nitroprusside and who exhibit signs of impaired oxygen delivery despite adequate cardiac output and adequate arterial pO2. Methemoglobinemic blood is chocolate brown, without the expected color change on exposure to air. Methemoglobin levels >10% are considered clinically significant.

When methemoglobinemia is diagnosed, the treatment of choice is 1-2 mg/kg of methylene blue, administered intravenously over several minutes.

5.5 Increased Intracranial Pressure

Like other vasodilators, sodium nitroprusside can cause increases in intracranial pressure.

5.6 Anemia and Hypovolemia with Anesthesia

When sodium nitroprusside (or any other vasodilator) is used for controlled hypotension during anesthesia, the patient’s capacity to compensate for anemia and hypovolemia may be diminished. If possible, correct pre-existing anemia and hypovolemia prior to administration.

6 ADVERSE REACTIONS

The following adverse reactions are described, or described in greater detail, in other sections:

- Hypotension [see Warnings and Precautions (5.1)]
- Cyanide Toxicity [see Warnings and Precautions (5.2)]
- Thiocyanate Toxicity [see Warnings and Precautions (5.3)]
- Methemoglobinemia [see Warnings and Precautions (5.4)]
- Increased Intracranial Pressure [see Warnings and Precautions (5.5)]
- Anemia and Hypovolemia [see Warnings and Precautions (5.6)]

Less common adverse reactions include:

Cardiovascular: Bradycardia, electrocardiographic changes, tachycardia, palpitations, retrosternal discomfort

Dermatologic: Rash

Endocrine: Hypothyroidism

Gastrointestinal: Ileus, nausea, abdominal pain

Hematologic: Decreased platelet aggregation

Musculoskelatal:Muscle twitching

Neurologic: Increased intracranial pressure, dizziness, headache

Miscellaneous: Flushing, diaphoresis, venous streaking, irritation at the infusion site

8 USE IN SPECIFIC POPULATIONS

8.1 Pregnancy

Risk Summary

Based on animal data and mechanism of action, sodium nitroprusside may lead to cyanide exposure and potential adverse effects in the fetus [see Clinical Pharmacology (12.3) and Clinical Considerations]. Published post-marketing reports with sodium nitroprusside use in pregnant women are insufficient to inform a drug-associated risk of adverse pregnancy related outcomes [see Data]. There were no animal reproduction studies conducted with sodium nitroprusside during pregnancy. However, there are published studies in pregnant sheep that demonstrate that nitroprusside crosses the placenta and that fetal cyanide levels were dose-related to maternal levels of sodium nitroprusside [see Data]. Advise pregnant women of the potential risk to a fetus.

The estimated background risk of major birth defects and miscarriage for the indicated population is unknown. All pregnancies have a background risk of birth defect, loss, or other adverse outcomes. In the U.S. general population, the estimated background risk of major birth defects and miscarriage in clinically recognized pregnancies is 2-4% and 15-20%, respectively.

Clinical Considerations

Fetal/Neonatal Adverse Reactions

Prolonged use and large doses of sodium nitroprusside during pregnancy may result in cyanide toxicity that may be fatal to the fetus. In the unusual case that there is no appropriate alternative to therapy with sodium nitroprusside for a particular patient, apprise the mother of the potential risk to the fetus [see Warnings and Precautions (5.2)].

Data

Human Data

A small number of cases have reported adverse events, including stillbirths, in pregnant women with severe pregnancy-induced hypertension who were treated with sodium nitroprusside. However, methodological limitations, including small sample size and limited information on sodium nitroprusside dosage and duration of treatment, as well as the cyanide concentration in maternal blood or fetal tissue, preclude a reliable evaluation of the potential risk of adverse fetal outcomes with the use of sodium nitroprusside during pregnancy.

Animal Data

In three studies in pregnant ewes, nitroprusside was shown to cross the placental barrier. Fetal cyanide levels were shown to be dose-related to maternal levels of nitroprusside. The metabolic transformation of sodium nitroprusside given to pregnant ewes led to fatal levels of cyanide in the fetuses. The infusion of 25 mcg/kg/min of sodium nitroprusside for one hour in pregnant ewes resulted in the death of all fetuses. Pregnant ewes infused with 1 mcg/kg/min of sodium nitroprusside for one hour delivered normal lambs.

8.2 Lactation

Risk Summary

There is no information about the presence of sodium nitroprusside in human milk, the effects on the breastfed infant, or the effects on milk production. Thiocyanate, one of sodium nitroprusside’s metabolites, is present in human milk. It is unclear how long, if ever, levels of thiocyanate in milk are clinically relevant.

8.4 Pediatric Use

Efficacy in the pediatric population was established based on adult trials and supported by the dose-ranging trial (Study 1) and an open label trial of at least 12 hour infusion at a rate that achieved adequate MAP control (Study 2) with pediatric patients on sodium nitroprusside. No novel safety issues were seen in these studies in pediatric patients [see Clinical Studies (14)].

10 OVERDOSAGE

Overdosage of nitroprusside can be manifested as excessive hypotension or cyanide toxicity [see Warnings and Precaution (5.1, 5.2)] or as thiocyanate toxicity [see Warnings and Precautions (5.3)]. Cyanide toxicity causes venous hyperoxemia with bright red venous blood. Cells become unable to extract the oxygen delivered to them, leading to air hunger, confusion and death. Lactic acidosis may occur, but its emergence may lag other life-threatening manifestations of cyanide toxicity.

Cyanide levels can be measured by many laboratories, and blood-gas studies that can detect venous hyperoxemia or acidosis are widely available. Acidosis may not appear until more than an hour after the appearance of dangerous cyanide levels. Suspicion of cyanide toxicity is adequate grounds for initiation of treatment.

Treatment of cyanide toxicity consists of:

- discontinuing sodium nitroprusside;
- administration of sodium nitrite to convert as much hemoglobin into methemoglobin as the patient can safely tolerate; and then
- infusing sodium thiosulfate to convert the cyanide into thiocyanate.

Hemodialysis is ineffective in removal of cyanide, but it will eliminate most thiocyanate.

Sodium nitrite is available in a 3% solution, and 4-6 mg/kg (about 0.2 mL/kg) should be injected over 2-4 minutes. This dose can be expected to convert about 10% of the patient’s hemoglobin into methemoglobin; this level of methemoglobinemia is not associated with any important hazard of its own.

Immediately after infusion of the sodium nitrite, sodium thiosulfate should be infused. This agent is available in 10% and 25% solutions, and the recommended dose is 150-200 mg/kg; a typical adult dose is 50 mL of the 25% solution. Thiosulfate treatment of an acutely cyanide-toxic patient will raise thiocyanate levels, but not to a dangerous degree.

The nitrite/thiosulfate regimen may be repeated, at half the original doses, after two hours.

Cyanide antidote kits are available.

11 DESCRIPTION

Sodium nitroprusside is disodium pentacyanonitrosylferrate(2-) dihydrate, a hypotensive agent whose structural formula is

Sodium Nitroprusside has molecular formula Na2[Fe(CN)5NO] • 2H2O and molecular weight of 297.95. Dry sodium nitroprusside is a reddish-brown powder, soluble in water.

Sodium nitroprusside solution is rapidly degraded by trace contaminants, often with resulting color changes [see Dosage and Administration (2.1)].

NIPRIDE® RTU is supplied as a sterile, unpreserved, colorless to red-brown solution packaged in a single-use 100-mL vial. Each 100 mL of solution in vial contains 50 mg of sodium nitroprusside (0.5 mg/mL), 900 mg of sodium chloride, USP (9 mg/mL), in sterile water for injection, USP.

NIPRIDE® RTU is also supplied as a sterile, unpreserved, colorless to red-brown solution packaged in a single-use 100-mL vial. Each 100 mL of solution in vial contains 20 mg of sodium nitroprusside (0.2 mg/mL), 900 mg of sodium chloride, USP (9 mg/mL), in sterile water for injection, USP.

NIPRIDE® RTU is also supplied as a sterile, unpreserved, colorless to red-brown solution packaged in a single-use 50-mL vial. Each 50 mL of solution in vial contains 10 mg of sodium nitroprusside (0.2 mg/mL), 450 mg of sodium chloride, USP (9 mg/mL), in sterile water for injection, USP.

12 CLINICAL PHARMACOLOGY

12.1 Mechanism of Action

Sodium nitroprusside interacts with oxyhemoglobin to produce methemoglobin, cyanide, and nitric oxide (NO). NO then reacts with guanylate cyclase in vascular smooth muscle to produce cGMP that reduces intracellular calcium concentrations resulting in relaxation of vascular smooth muscle and consequent dilatation of peripheral arteries and veins. Other smooth muscle (e.g., uterus, duodenum) is not affected. Sodium nitroprusside is more active on veins than on arteries, but this selectivity is much less marked than that of nitroglycerin. Dilatation of the veins promotes peripheral pooling of blood and decreases venous return to the heart, thereby reducing left ventricular end diastolic pressure and pulmonary capillary wedge pressure (preload). Arteriolar relaxation reduces systemic vascular resistance, systolic arterial pressure, and mean arterial pressure (afterload). Dilatation of the coronary arteries also occurs.

12.2 Pharmacodynamics

In association with the decrease in blood pressure, sodium nitroprusside administered intravenously to hypertensive and normotensive patients produces slight increases in heart rate and a variable effect on cardiac output. In hypertensive patients, moderate doses induce renal vasodilatation roughly proportional to the decrease in systemic blood pressure, so there is no appreciable change in renal blood flow or glomerular filtration rate.

The hypotensive effect of sodium nitroprusside is seen within a minute or two after the start of an adequate infusion, and it dissipates almost as rapidly after an infusion is discontinued. The effect is augmented by ganglionic blocking agents and inhaled anesthetics.

12.3 Pharmacokinetics

Infused sodium nitroprusside is rapidly distributed to a volume that is approximately coextensive with the extracellular space. The drug is cleared by intraerythrocytic reaction with hemoglobin (Hgb), and sodium nitroprusside’s resulting circulatory half-life is about 2 minutes.

The products of the nitroprusside/hemoglobin reaction are cyanmethemoglobin (cyanmetHgb) and cyanide ion (CN¯).

Metabolism

As shown in the diagram below, the essential features of nitroprusside metabolism are:

- one molecule of sodium nitroprusside is metabolized by combination with hemoglobin to produce one molecule of cyanmethemoglobin and four CN¯ ions;
- methemoglobin, obtained from hemoglobin, can sequester cyanide as cyanmethemoglobin;
- thiosulfate reacts with cyanide to produce thiocyanate;
- thiocyanate is eliminated in the urine;
- cyanide not otherwise removed binds to cytochromes; and
- cyanide is much more toxic than methemoglobin or thiocyanate.

Cyanide ion is normally found in serum; it is derived from dietary substrates and from tobacco smoke. CN¯ levels in packed erythrocytes are typically less than 1 μmol/L (less than 25 mcg/L); levels are roughly doubled in heavy smokers.

At healthy steady state, most people have less than 1% of their hemoglobin in the form of methemoglobin. Nitroprusside metabolism can lead to methemoglobin formation. Relatively large quantities of sodium nitroprusside, however, are required to produce significant methemoglobinemia.

At physiologic methemoglobin levels, the CN¯ binding capacity of packed red cells is a little less than 200 μmol/L (5 mg/L). Cytochrome toxicity is seen at levels only slightly higher, and death has been reported at levels from 300 to 3000 μmol/L (8–80 mg/L). A patient with a normal redcell mass (35 mL/kg) and normal methemoglobin levels can buffer about 175 mcg/kg of CN¯, corresponding to a little less than 500 mcg/kg of infused sodium nitroprusside.

Thiocyanate (SCN¯) is a normal physiological constituent of serum, with normal levels typically in the range of 50-250 μmol/L (3-15 mg/L). Clearance of SCN¯ is primarily renal. In renal failure, the half-life can be doubled or tripled.

When thiosulfate is being supplied only by normal physiologic mechanisms, conversion of CN¯ to SCN¯ generally proceeds at about 1 mcg/kg/min. This rate of CN¯ clearance corresponds to steady-state processing of a sodium nitroprusside infusion of slightly more than 2 mcg/kg/min. CN¯ begins to accumulate when sodium nitroprusside infusions exceed this rate.

13 NONCLINICAL TOXICOLOGY

13.1 Carcinogenesis, Mutagenesis, Impairment of Fertility

Animal studies assessing sodium nitroprusside’s carcinogenicity and mutagenicity have not been conducted. Similarly, sodium nitroprusside has not been tested for effects on fertility.

13.2 Animal Toxicology and/or Pharmacology

The acute intravenous mean lethal doses (LD50) of nitroprusside in rabbits, dogs, mice, and rats are 2.8, 5.0, 8.4, and 11.2 mg/kg, respectively.

14 CLINICAL STUDIES

Baseline-controlled clinical trials have uniformly shown that sodium nitroprusside has a prompt hypotensive effect, at least initially, in all populations. With increasing rates of infusion, sodium nitroprusside has been able to lower blood pressure without an observed limit of effect.

Clinical trials have also shown that the hypotensive effect of sodium nitroprusside is associated with reduced blood loss in a variety of major surgical procedures.

In patients with acute heart failure and increased peripheral vascular resistance, administration of sodium nitroprusside causes reductions in peripheral resistance, increases in cardiac output, and reductions in left ventricular filling pressure.

Progressive tachyphylaxis to the hypotensive effects of sodium nitroprusside has been reported in several trials and numerous case reports. The mechanism of tachyphylaxis to sodium nitroprusside remains unknown.

Pediatric

The effects of sodium nitroprusside to induce hypotension were evaluated in two trials in pediatric patients less than 17 years of age. In both trials, at least 50% of the patients were pre-pubertal, and about 50% of these pre-pubertal patients were less than 2 years of age, including 4 neonates. The primary efficacy variable was the mean arterial pressure (MAP).

There were 203 pediatric patients in a parallel, dose-ranging study (Study 1). During the 30-minute blinded phase, patients were randomized 1:1:1:1 to receive sodium nitroprusside 0.3, 1, 2, or 3 mcg/kg/min. The infusion rate was increased step-wise to the target dose rate (i.e., 1/3 of the full rate for the first 5 minutes, 2/3 of the full rate for the next 5 minutes, and the full dose rate for the last 20 minutes). If the investigator believed that an increase to the next higher dose rate would be unsafe, the infusion remained at the current rate for the remainder of the blinded infusion. Since there was no placebo group, the change from baseline likely overestimates the true magnitude of blood pressure effect. Nevertheless, MAP decreased 11 to 20 mmHg from baseline across the four doses (Table 1).

There were 63 pediatric patients in a long-term infusion trial (Study 2). During an open-label phase (12 to 24 hours), sodium nitroprusside was started at 0.3 mcg/kg/min and titrated according to the BP response.

Patients were then randomized to placebo or to continuing the same dose of sodium nitroprusside. The average MAP was greater in the control group than in the sodium nitroprusside group for every time point during the blinded withdrawal phase, demonstrating that sodium nitroprusside is effective for at least 12 hours.

In both studies, similar effects on MAP were seen in all age groups.

Table 1: Change from Baseline in MAP (mmHg) After 30 Minutes Double-Blind Infusion (Study 1)
 | Dose (mcg/kg/min)
Endpoint | 0.3 | 1 | 2 | 3
 | (N = 50) | (N = 49) | (N = 53) | (N = 51)
Baseline | 76 ± 11 | 77 ± 15 | 74 ± 12 | 76 ± 12
30 Min | 65 ± 13 | 60 ± 15 | 54 ± 12 | 60 ± 18
Change from | -11 ± 16 | -17 ± 13 | -20 ± 16 | -17 ± 19
Baseline | (-15, -6.5) | (-21, -13) | (-24, -13) | (-22, -11)
Mean ± SD (95% CI)

16 HOW SUPPLIED/STORAGE AND HANDLING

NIPRIDE®RTU is supplied in amber-colored, single-dose, 50 mg/100 mL (0.5 mg/mL) Fliptop Vials (NDC 51754-1006-1), 20 mg/100 mL (0.2 mg/mL) Fliptop Vials (NDC 51754-1029-1) and 10 mg/50 mL (0.2 mg/mL) Fliptop Vials (NDC 51754-1018-1).

Store at 20° to 25°C (68° to 77°F) [See USP Controlled Room Temperature].

To protect NIPRIDE®RTU from light, vial should be stored in its carton until used.

17 PATIENT COUNSELING INFORMATION

Pregnancy

Inform female patients of reproductive potential that Sodium Nitroprusside Injection may cause fetal harm and to inform their prescriber of a known or suspected pregnancy [see Use in Specific Population (8.1)].

Manufactured and Distributed by:

Exela Pharma Sciences, LLC
Lenoir, NC 28645

PACKAGE/LABEL PRINCIPAL DISPLAY PANEL- 0.5 mg/mL in 100 mL Vial Label

Rx Only NDC 51754-1006-1

NIPRIDE® RTU

SODIUM NITROPRUSSIDE

in 0.9% Sodium Chloride Injection

(Ready to Use)

50 mg/100mL (0.5 mg/mL)

For Intravenous Infusion Only

100 mL Single Dose Vial. Discard unused portion.

PACKAGE/LABEL PRINCIPAL DISPLAY PANEL-0.5 mg/mL in 100 mL Carton

Rx Only NDC 51754-1018-1

NIPRIDE RTU

SODIUM NITROPRUSSIDE

in 0.9% Sodium Chloride Injection

(Ready to Use)

10 mg/50mL (0.2 mg/mL)

For Intravenous Infusion Only

50 mL Single Dose Vial

PACKAGE/LABEL PRINCIPAL DISPLAY PANEL-0.2 mg/mL in 50 mL Vial Label

NDC 51754-1018-1 Rx Only

NIPRIDE® RTU

SODIUM NITROPRUSSIDE

in 0.9% Sodium Chloride Injection

(Ready to Use)

10 mg/50mL (0.2 mg/mL)

For Intravenous Infusion Only

50 mL Single Dose Vial. Discard unused portion.

PACKAGE/LABEL PRINCIPAL DISPLAY PANEL0.2 mg/mL in 50 mL Carton

NDC 51754-1018-1 Rx Only

NIPRIDE® RTU

SODIUM NITROPRUSSIDE

in 0.9% Sodium Chloride Injection

(Ready to Use)

10 mg/50mL (0.2 mg/mL)

For Intravenous Infusion Only

50 mL Single Dose Vial.

PACKAGE/LABEL PRINCIPAL DISPLAY PANEL-0.2 mg/mL in 20 mL Vial Label

NDC 51754-1029-1 Rx Only

NIPRIDE® RTU

SODIUM NITROPRUSSIDE

in 0.9% Sodium Chloride Injection

(Ready to Use)

20 mg/100mL (0.2 mg/mL)

For Intravenous Infusion Only

100 mL Single Dose Vial. Discard unused portion.

PACKAGE/LABEL PRINCIPAL DISPLAY PANEL-0.2 mg/mL in 20 mL Carton

NDC 51754-1029-1 Rx Only

NIPRIDE® RTU

SODIUM NITROPRUSSIDE

in 0.9% Sodium Chloride Injection

(Ready to Use)

20 mg/100mL (0.2 mg/mL)

For Intravenous Infusion Only

100 mL Single Dose Vial.

Discard unused portion.